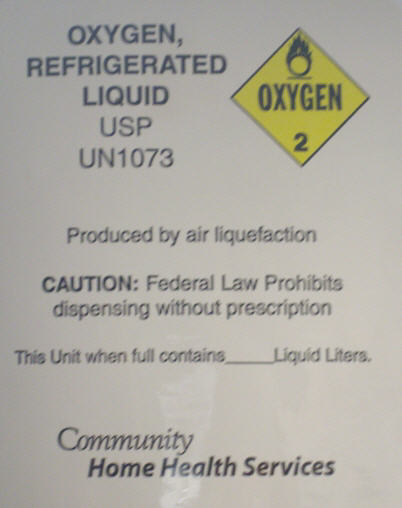 DRUG LABEL: Liquid Oxygen
NDC: 65360-1073 | Form: GAS
Manufacturer: Community Home Health Services
Category: prescription | Type: HUMAN PRESCRIPTION DRUG LABEL
Date: 20090928

ACTIVE INGREDIENTS: OXYGEN 995 mL/1 L

Liquid Oxygen

PRINCIPAL DISPLAY PANEL

Oxygen, Refrigerated Liquid USP
UN1073

Produced by air liquefaction

CAUTION: Federal Law Prohibits dispensing without prescription

This Unit when full contains __ Liquid Liters.